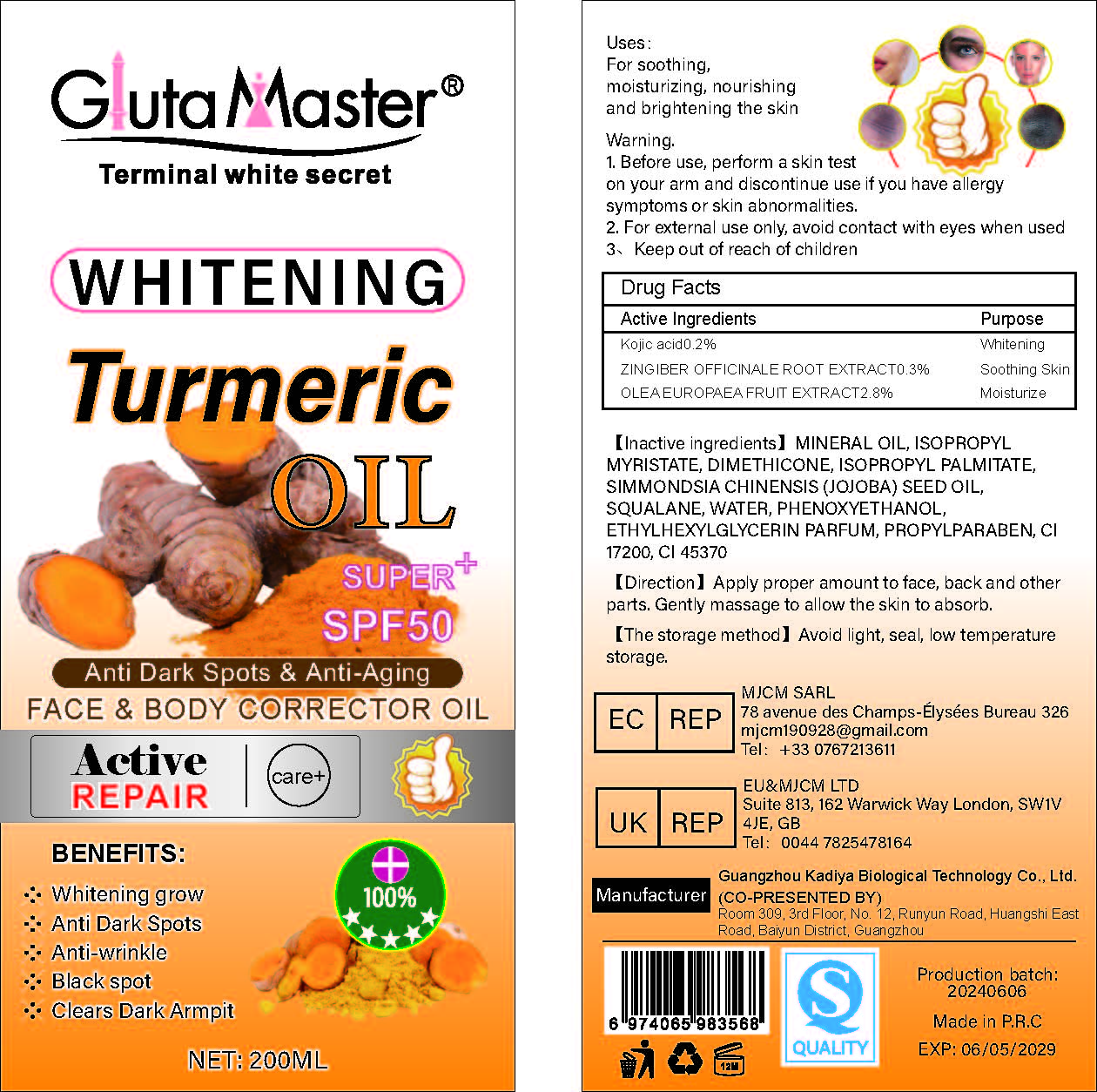 DRUG LABEL: Whitening Turmeric Oil
NDC: 84423-003 | Form: OIL
Manufacturer: Guangzhou Kadiya Biotechnology Co. Ltd.
Category: otc | Type: HUMAN OTC DRUG LABEL
Date: 20240627

ACTIVE INGREDIENTS: KOJIC ACID 0.4 mg/200 mg; OLIVE OIL 5.6 mg/200 mg
INACTIVE INGREDIENTS: GINGER; D&C RED NO. 33; ISOPROPYL MYRISTATE; ETHYLHEXYLGLYCERIN; WATER; SOLVENT RED 72; SQUALANE; JOJOBA OIL; PHENOXYETHANOL; DIMETHICONE 350; ISOPROPYL PALMITATE; PROPYLPARABEN; MINERAL OIL

ACTIVE INGREDIENT

Kojic acid 0.2%

OLEA EUROPAEA (OLIVE) FRUIT OIL 2.8%

Inactive ingredients

MINERAL OIL，ISOPROPYL MYRISTATE，DIMETHICONE，ISOPROPYL PALMITATE，SIMMONDSIA CHINENSIS (JOJOBA) SEED OIL，SQUALANE，WATER，PHENOXYETHANOL，ETHYLHEXYLGLYCERIN PARFUM，PROPYLPARABEN，CI 17200，CI 45370

PURPOSE

For soothing, moisturizing, nourishing and brightening the skin

WARNINGS

1.Before use, perform a skin test on your arm and discontinue use if you have allergy symptoms or skin abnormalities.
2、For external use only, avoid contact with eyes when used
3、Keep out of reach of children

Instructions for use

Apply to face, back and other parts, Gently massage to allow the skin to absorb.

Dosage

Apply proper amount to face, back and otherparts, Gently massage to allow the skin to absorb.

Warning

Keep out of reach of children

PACKAGE LABEL

WHITENING Turmeric OIL

1.Purpose

For soothing, moisturizing, nourishing and brightening the skin

2. Warning

1.)Before use, perform a skin test on your arm and discontinue use if you have allergy symptoms or skin abnormalities.

2.) For external use only, avoid contact with eyes when use

3.)Keep out of reach of children

3 Active ingredints

Kojic acid0.2%

ZINGIBER OFFICINALE ROOT EXTRACTO.3%

OLEA EUROPAEA FRUIT EXTRACT2.8%

4.Inactive ingredients: MINERAL OIL, ISOPROPYL MYRISTATE, DIMETHICONE, ISOPROPYL PALMITATE, SIMMONDSIA CHINENSIS (JOJOBA) SEED OIL, SQUALANE, WATER, PHENOXYETHANOL,ETHYLHEXYLGLYCERIN PARFUM, PROPYLPARABEN, CI17200, CI 45370

5.Instructions for use

Apply proper amount to face, back and other parts. Gently massage to allow the skin to absorb.